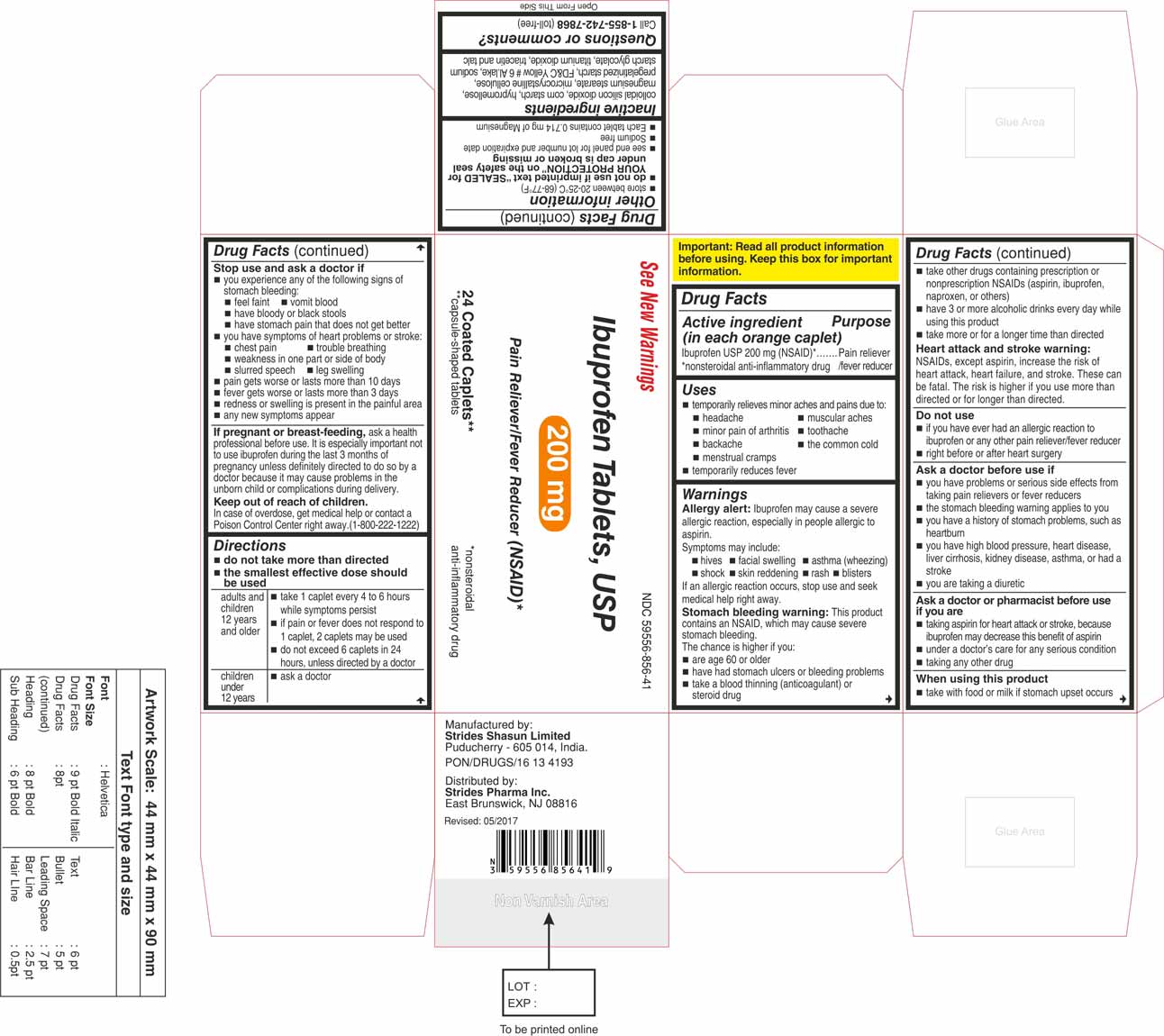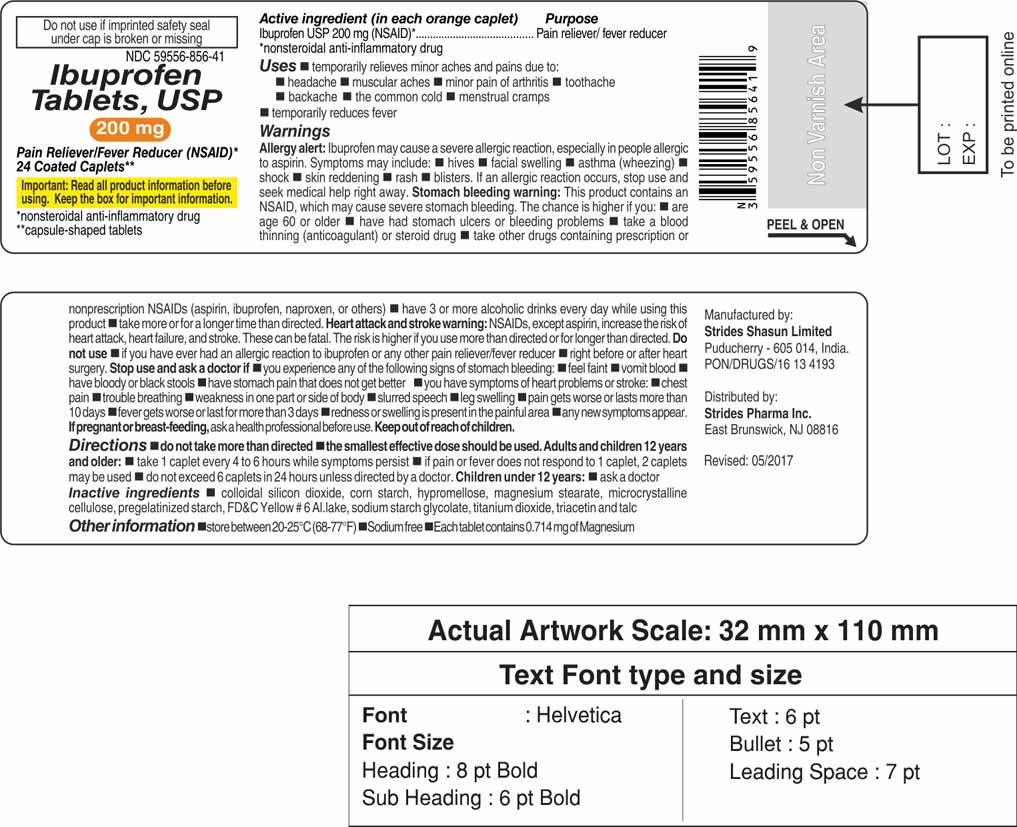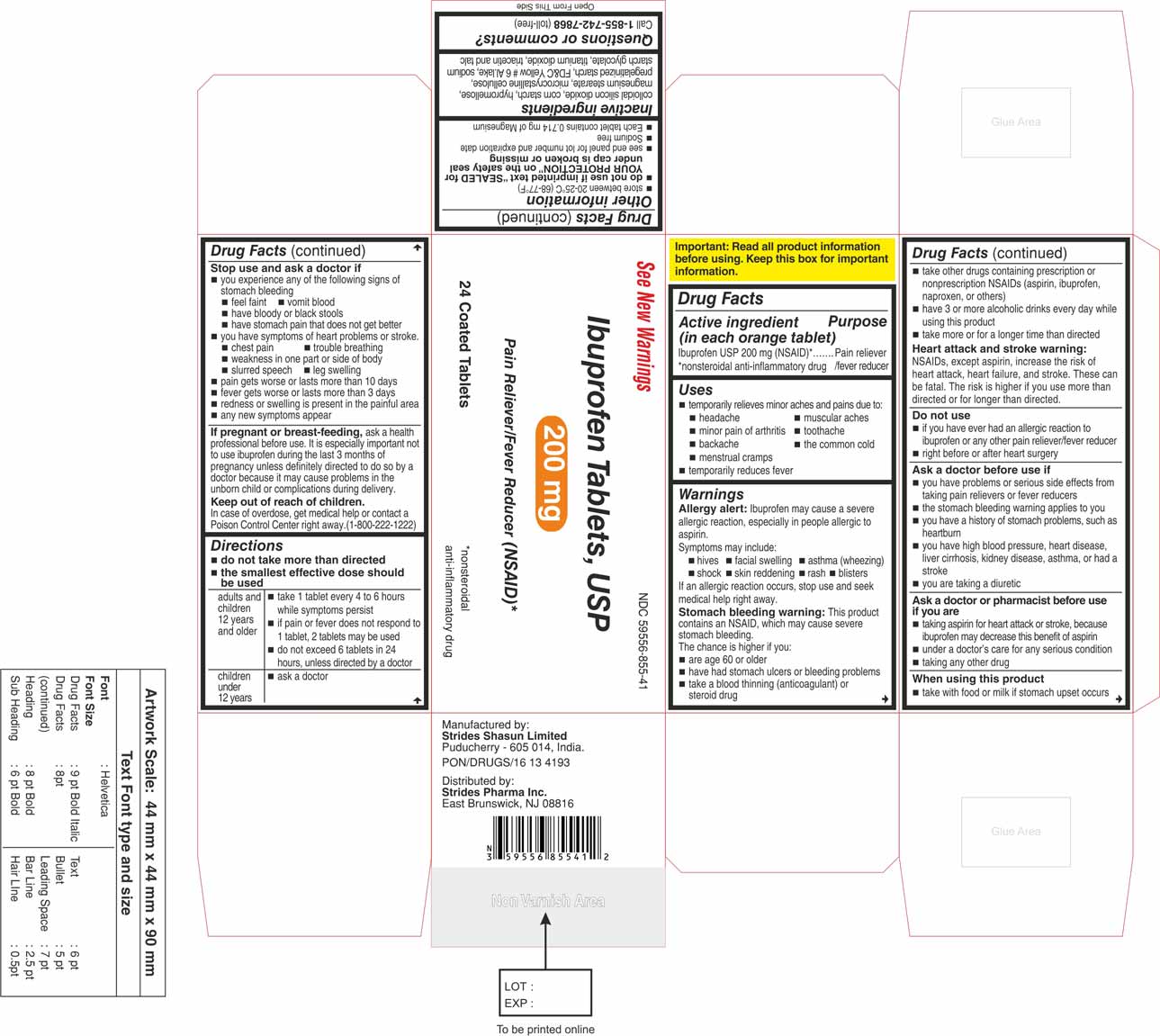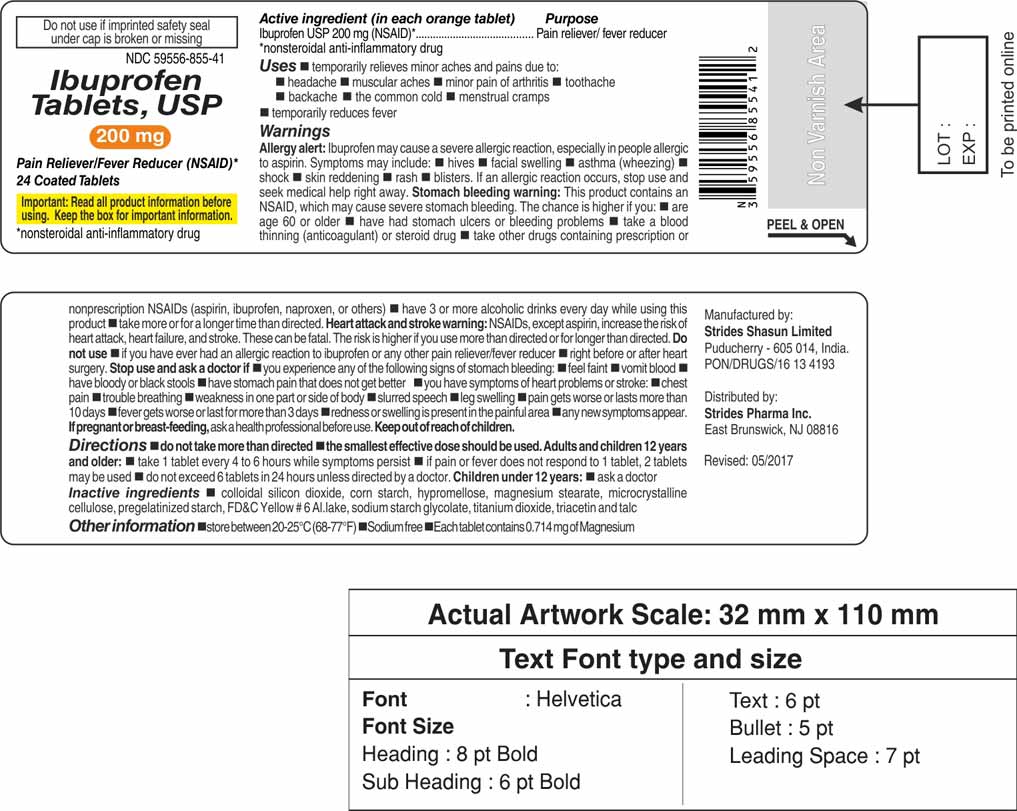 DRUG LABEL: Ibuprofen
NDC: 59556-856 | Form: TABLET, COATED
Manufacturer: Strides Pharma Inc.
Category: otc | Type: Human OTC Drug Label
Date: 20170526

ACTIVE INGREDIENTS: IBUPROFEN 200 mg/1 1
INACTIVE INGREDIENTS: SILICON DIOXIDE; MAGNESIUM STEARATE; CELLULOSE, MICROCRYSTALLINE; STARCH, CORN; SODIUM STARCH GLYCOLATE TYPE A POTATO; HYPROMELLOSES; TITANIUM DIOXIDE; TRIACETIN; FD&C YELLOW NO. 6; TALC

Drugs Facts

ACTIVE INGREDIENT(S)

(ineach orange tablet or caplet**)

Ibuprofen USP 200 mg (NSAID)*

*nonsteroidal anti-inflammatory drug

**capsule-shaped tablets

PURPOSE

Pain reliever/fever reducer

USE(S)

- temporarily relieves minor aches and pains due to:
  - headache
  - muscular aches
  - minor pain of arthritis
  - toothache
  - backache
  - the common cold
  - menstrual cramps
- temporarily reduces fever

WARNINGS

Allergy alert:
Ibuprofen USP may cause a severe allergic reaction, especially in people allergic to aspirin. Symptoms may include:

- hives
- facial swelling
- asthma (wheezing)
- shock
- skin reddening
- rash
- blisters

If an allergic reaction occurs, stop use and seek medical help right away.
Stomach bleeding warning
This product contains an NSAID, which may cause severe stomach bleeding. The chance is higher if you:

- are age 60 or older
- have had stomach ulcers or bleeding problems
- take a blood thinning (anticoagulant) or steroid drug
- take other drugs containing prescription or non prescription NSAIDs (aspirin, ibuprofen, naproxen, or others)
- have 3 or more alcoholic drinks every day while using this product
- take more or for a longer time than directed.

Heart attack and stroke warning: NSAIDs, except aspirin, increase the risk of heart failure, and stroke. these can be fatal. The risk is higher if you use more than directed or for longer than directed.

DO NOT USE

- if you have ever had an allergic reaction to ibuprofen or any other pain reliever / fever reducer
- right before or after heart surgery

ASK A DOCTOR BEFORE USE IF

- you have problems or serious side effects from taking pain relievers or fever reducers
- the stomach bleeding warning applies to you
- you have a history of stomach problems, such ad heartburn
- you have high blood pressure, heart disease, liver cirrhosis, kidney disease, asthma or had a stroke
- you are taking a diuretic

ASK A DOCTOR OR PHARMACIST BEFORE USE IF

- taking aspirin for heart attack or stroke, because ibuprofen USP may decrease this benefit of aspirin
- under a doctor's care for any serious condition
- taking any other drug

WHEN USING THIS PRODUCT

- take with food or milk if stomach upset occurs
- the risk of heart attack or stroke may increase if you use more than directed or for longer than directed

STOP USE AND ASK DOCTOR IF

- you experience any of the following signs of stomach bleeding
  - feel faint
  - vomit blood
  - have bloody or black stools
  - have stomach pain that does not get better
- you have symptoms of heart problems or stroke:
  - chest pain
  - trouble in breathing
  - weakness in one part or side of body
  - slurred speech
  - leg swelling
- pain gets worse or lasts more than 10 days
- fever gets worse or lasts more than 3 days
- redness or swelling is present in the painful area
- any new symptoms appear

If pregnant or breast-feeding, ask a health care professional before use. it is especially important not to use ibuprofen USP
during the last 3 months of pregnancy unless definitely directed to do so by a doctor because it may cause problems in the unborn child
or complications during delivery.

KEEP OUT OF REACH OF CHILDREN

In case of overdose, get medical help or contact a poison control centre (1-800-222-1222) right away.

DIRECTIONS

- do not take more than directed
- the smallest effective dose should be used
  adults and children 12 years and older | - take 1 tablet or caplet every 4 to 6 hours while symptoms persist - if pain or fever does not respond to 1 tablet or caplet, 2 tablets or caplets may be used - do not exceed 6 tablets or caplets in 24 hours, unless directed by a doctor
  children under 12 years | - ask a doctor
  OTHER INFORMATION
- store between 20°-25°C (68° - 77°F)
- do not use if imprinted text "SEALED FOR YOUR PROTECTION" on the safety seal under cap is broken or missing
- Sodium free
- Each tablet contains 0.714 mg of Magnesium
- see end panel for lot number and expiration date.

INACTIVE INGREDIENTS (S)

colloidal silicon dioxide, corn starch, hypromellose, magnesium stearate, microcrystalline cellulose, pregelatinized starch, red iron oxide, sodium starch glycolate, talc, titanium dioxide and triacetin
QUESTIONS OR COMMENTS?
Call 1-855-742-7868 (toll-free): weekdays 8.00 AM to 8.00 PM EST
Manufactured by:
Strides Shasun Limited,
Puducherry - 605 014, India.
PON/DRUGS/16134193
Distributed by:
Strides Pharma Inc.
East Brunswick, NJ 08816
May 2017

PRINCIPAL DISPLAY PANEL

Package Label (Caplet Shaped Tablets) - Principal Display Panel - 24 - Count Bottle, 200 mg Tablets

See New Warnings

NDC 59556-856-41

Ibuprofen Tablets, USP

200 mg

Pain Reliever/Fever Reducer (NSAID)*

24 Coated Caplets**

**capsule-shaped tablets

*nonsteroidal anti-inflammatory drug

Package Label (Round Shaped Tablets) - Principal Display Panel - 24 - Count Bottle, 200 mg Tablets

See New Warnings

NDC 59556-855-41

Ibuprofen Tablets, USP

200 mg

Pain Reliever/Fever Reducer (NSAID)*

24 Coated Tablets

*nonsteroidal anti-inflammatory drug